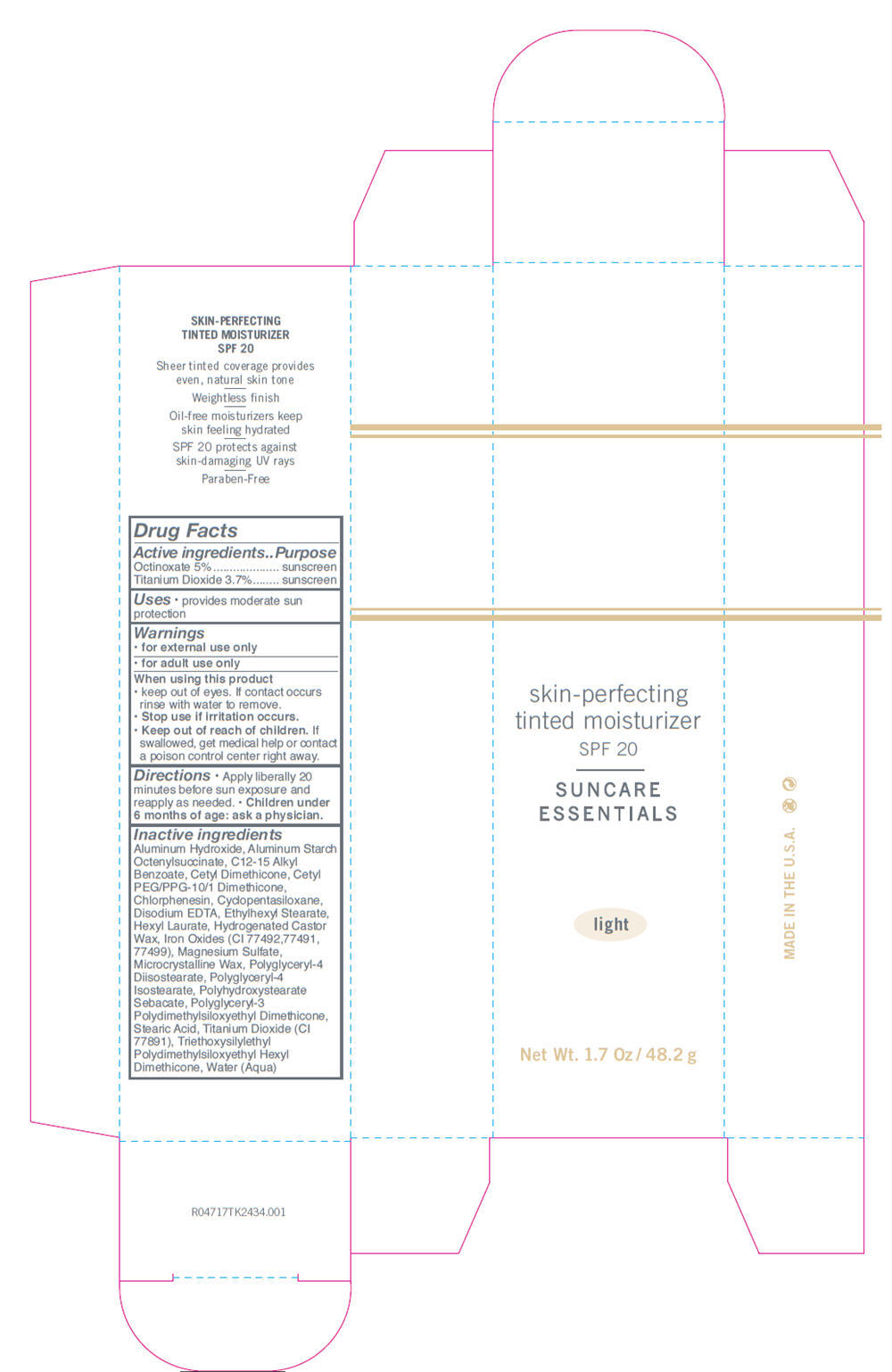 DRUG LABEL: Tinted Moisturizer SPF20 
NDC: 24623-047 | Form: CREAM
Manufacturer: CBI Laboratories, Inc
Category: otc | Type: HUMAN OTC DRUG LABEL
Date: 20110105

ACTIVE INGREDIENTS: OCTINOXATE 0.05 g/1 g; TITANIUM DIOXIDE 0.037 g/1 g
INACTIVE INGREDIENTS: POLYGLYCERYL-4 ISOSTEARATE; ETHYLHEXYL STEARATE; WATER; CYCLOMETHICONE; C12-15 ALKYL BENZOATE; HYDROGENATED CASTOR OIL; MICROCRYSTALLINE WAX; FERRIC OXIDE RED; FERROSOFERRIC OXIDE; FERRIC OXIDE YELLOW; CHLORPHENESIN; MAGNESIUM SULFATE, UNSPECIFIED; EDETATE DISODIUM; STEARIC ACID

skin-perfecting
tinted moisturizer
SPF 20
SUNCARE
ESSENTIALS
light

Drug Facts

Active ingredients | Purpose
Octinoxate 5% | sunscreen
Titanium Dioxide 3.7% | sunscreen

Uses

- provides moderate sun protection

Warnings

- for external use only
- for adult use only

When using this product

- keep out of eyes. If contact occurs rinse with water to remove.

- Stop use if irritation occurs.

- Keep out of reach of children. If swallowed, get medical help or contact a poison control center right away.

Directions

- Apply liberally 20 minutes before sun exposure and reapply as needed.
- Children under 6 months of age: ask a physician.

Inactive ingredients

Aluminum Hydroxide, Aluminum Starch Octenylsuccinate, C12-15 Alkyl Benzoate, Cetyl Dimethicone, Cetyl PEG/PPG-10/1 Dimethicone, Chlorphenesin, Cyclopentasiloxane, Disodium EDTA, Ethylhexyl Stearate, Hexyl Laurate, Hydrogenated Castor Wax, Iron Oxides (CI 77492,77491, 77499), Magnesium Sulfate, Microcrystalline Wax, Polyglyceryl-4 Diisostearate, Polyglyceryl-4 Isostearate, Polyhydroxystearate Sebacate, Polyglyceryl-3 Polydimethylsiloxyethyl Dimethicone, Stearic Acid, Titanium Dioxide (CI 77891), Triethoxysilylethyl Polydimethylsiloxyethyl Hexyl Dimethicone, Water (Aqua)

PRINCIPAL DISPLAY PANEL - 48.2 g Carton

skin-perfecting
tinted moisturizer
SPF 20

SUNCARE
ESSENTIALS

light

Net Wt. 1.7 Oz / 48.2 g